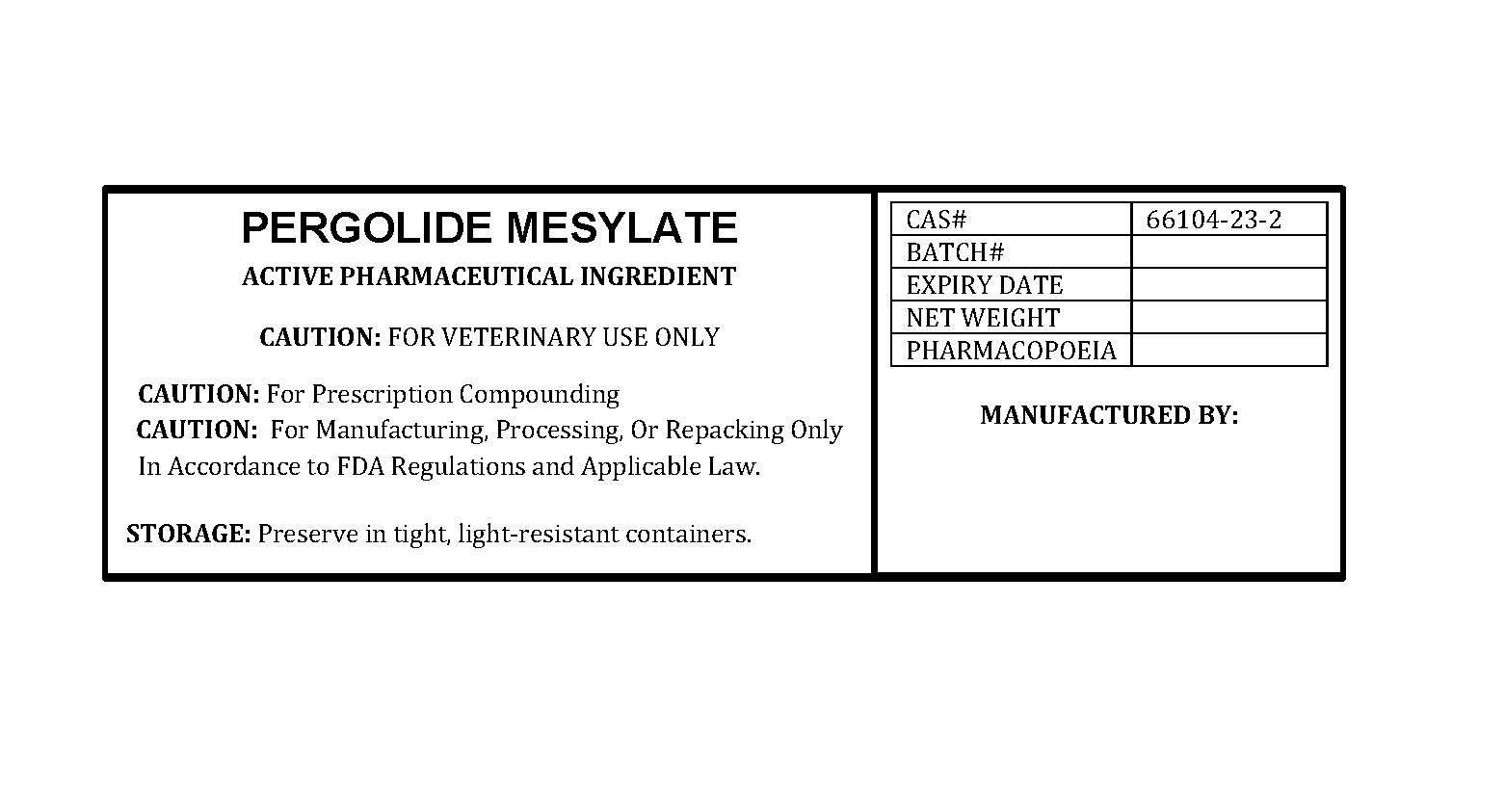 DRUG LABEL: PERGOLIDE MESYLATE
NDC: 86184-305 | Form: POWDER
Manufacturer: MAEDA INC
Category: other | Type: BULK INGREDIENT - ANIMAL DRUG
Date: 20250820

ACTIVE INGREDIENTS: PERGOLIDE MESYLATE 1 g/1 g

PERGOLIDE MESYLATE

PACKAGE LABEL

pergolidemesylatelabelfile.jpg